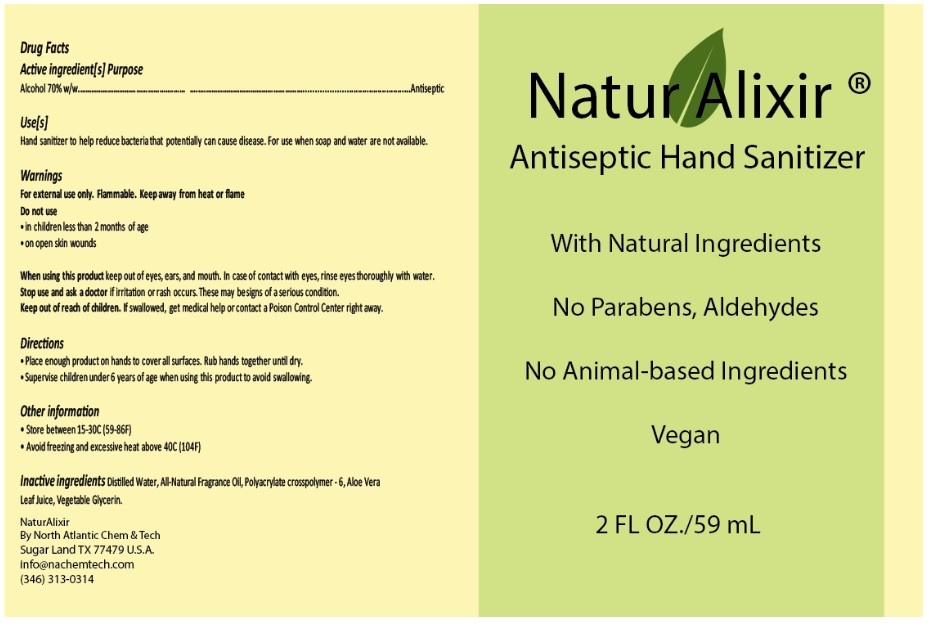 DRUG LABEL: NaturAlixir
NDC: 73835-001 | Form: GEL
Manufacturer: North Atlantic Chemicals and Technologies LLC
Category: otc | Type: HUMAN OTC DRUG LABEL
Date: 20200409

ACTIVE INGREDIENTS: ALCOHOL 70 mL/100 mL
INACTIVE INGREDIENTS: WATER; AMMONIUM ACRYLOYLDIMETHYLTAURATE, DIMETHYLACRYLAMIDE, LAURYL METHACRYLATE AND LAURETH-4 METHACRYLATE COPOLYMER, TRIMETHYLOLPROPANE TRIACRYLATE CROSSLINKED (45000 MPA.S); ALOE VERA LEAF; GLYCERIN

NaturAlixir

Active ingredient(s)

Alcohol 70% w/w

Purpose

Antiseptic

Use(s)

Hand sanitizer to help reduce bacteria that potentially can cause disease. For use when soap and water are not available.

Warnings

For external use only. Flammable. Keep away from heat or flame

Do not use

- in children less than 2 months of age
- on open skin wounds

When using this product keep out of eyes, ears and mouth. In case of contact with eye, rinse eyes thoroughly with water.

Stop use and see a doctor if irritation or rash occurs. These may be signs of a serious condition.

Keep out of reach of children. If swallowed, get medical help or contact a Poison Control Center right away.

Directions

- Place enough product on hands to cover all surfaces. Rub hands together until dry.
- Supervise children under 6 years of age when using this product to avoid swallowing.

Other information

- Store between 15-30°C (59-86°F)
- Avoid freezing and excessive heat above 40°C (104°F)

INACTIVE INGREDIENT

Inactive ingredients Distilled Water, All-Natural Fragrance Oil, Polyacrylate crosspolymer-6, Aloe Vera Leaf Juice, Vegetable Glycerin.

With Natural Ingredients

No Parabens, Aldehydes

No Animal-based Ingredients

Vegan